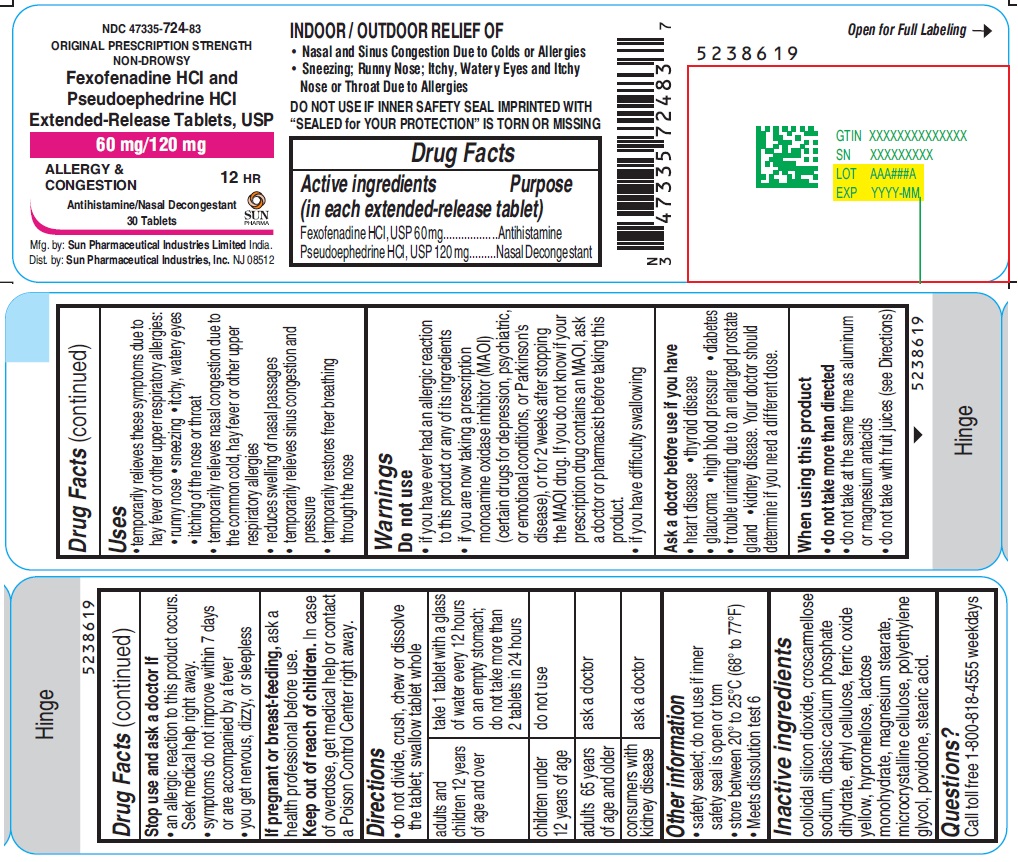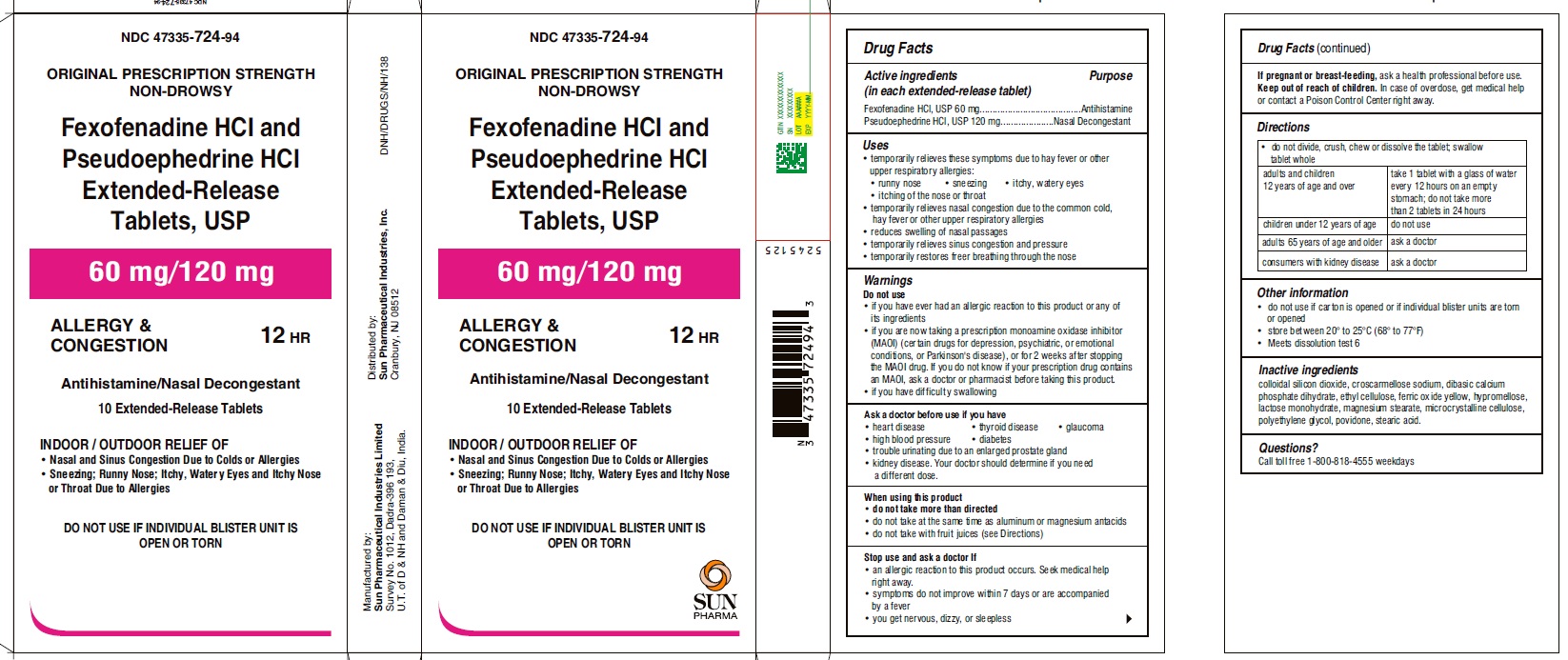 DRUG LABEL: Fexofenadine Hydrochloride and Pseudoephedrine Hydrochloride
NDC: 47335-724 | Form: TABLET, FILM COATED, EXTENDED RELEASE
Manufacturer: Sun Pharmaceutical Industries, Inc.
Category: otc | Type: Human OTC Drug Label
Date: 20250311

ACTIVE INGREDIENTS: FEXOFENADINE HYDROCHLORIDE 60 mg/1 1; PSEUDOEPHEDRINE HYDROCHLORIDE 120 mg/1 1
INACTIVE INGREDIENTS: LACTOSE MONOHYDRATE; CELLULOSE, MICROCRYSTALLINE; CROSCARMELLOSE SODIUM; POVIDONE K30; MAGNESIUM STEARATE; DIBASIC CALCIUM PHOSPHATE DIHYDRATE; SILICON DIOXIDE; ETHYLCELLULOSES; FERRIC OXIDE YELLOW; STEARIC ACID; HYPROMELLOSES; POLYETHYLENE GLYCOL, UNSPECIFIED

Fexofenadine Hydrochloride and Pseudoephedrine Hydrochloride Extended-Release Tablets, 60 mg/120 mg

Active ingredient(s)

(in each extended-release tablet)
Fexofenadine HCl, USP 60 mg
Pseudoephedrine HCl, USP 120 mg

Purpose

Antihistamine
Nasal Decongestant

Uses

- temporarily relieves these symptoms due to hay fever or other upper respiratory allergies:
  - runny nose
  - sneezing
  - itchy, watery eyes
  - itching of the nose or throat
- temporarily relieves nasal congestion due to the common cold, hay fever or other upper respiratory allergies
- reduces swelling of nasal passages
- temporarily relieves sinus congestion and pressure
- temporarily restores freer breathing through the nose

Do not use

- if you have ever had an allergic reaction to this product or any of its ingredients
- if you are now taking a prescription monoamine oxidase inhibitor (MAOI) (certain drugs for depression, psychiatric, or emotional conditions, or Parkinson’s disease), or for 2 weeks after stopping the MAOI drug. If you do not know if your prescription drug contains an MAOI, ask a doctor or pharmacist before taking this product.
- if you have difficulty swallowing

Ask a doctor before use if you have

- heart disease
- thyroid disease
- glaucoma
- high blood pressure
- diabetes
- trouble urinating due to an enlarged prostate gland
- kidney disease. Your doctor should determine if you need a different dose.

When using this product

- do not take more than directed
- do not take at the same time as aluminum or magnesium antacids
- do not take with fruit juices (see Directions)

Stop use and ask doctor if

- an allergic reaction to this product occurs. Seek medical help right away.
- symptoms do not improve within 7 days or are accompanied by a fever
- you get nervous, dizzy, or sleepless

If pregnant or breast-feeding

ask a health professional before use.

Keep out of reach of children

In case of overdose, get medical help or contact a Poison Control Center right away.

Directions

- do not divide, crush, chew or dissolve the tablet; swallow tablet whole

adults and children 12 years of age and over | take 1 tablet with a glass of water every 12 hours on an empty stomach; do not take more than 2 tablets in 24 hours
children under 12 years of age | do not use
adults 65 years of age and older | ask a doctor
consumers with kidney disease | ask a doctor

Other information

- safety sealed; do not use if inner safety seal is open or torn
- store between 20° to 25°C (68° to 77°F)
- Meets dissolution test 6

Inactive ingredients

colloidal silicon dioxide, croscarmellose sodium, dibasic calcium phosphate dihydrate, ethyl cellulose, ferric oxide yellow, hypromellose, lactose monohydrate, magnesium stearate, microcrystalline cellulose, polyethylene glycol, povidone, stearic acid.

Questions?

Call toll free 1-800-818-4555 weekdays

Principal Display Panel

NDC 47335-724-83

ORIGINAL PRESCRIPTION STRENGTH
NON-DROWSY
Fexofenadine HCl and Pseudoephedrine HCl Extended-Release Tablets, USP
60 mg/120 mg
ALLERGY &
CONGESTION
12 HR
Antihistamine/Nasal Decongestant
Indoor and Outdoor Allergies
30 Tablets
SUN PHARMA

Principal Display Panel-Showbox

NDC 47335-724-94
ORIGINAL PRESCRIPTION STRENGTH NON-DROWSY
Fexofenadine HCI and Pseudoephedrine HCI Extended-Release Tablets, USP
60 mg/120 mg
ALLERGY & CONGESTION
12 HR
Antihistamine/Nasal Decongestant
10 Extended-Release Tablets
INDOOR / OUTDOOR RELIEF OF
• Nasal and Sinus Congestion Due to Colds or Allergies
• Sneezing; Runny Nose; Itchy, Watery Eyes and Itchy Nose or Throat Due to Allergies
DO NOT USE IF INDIVIDUAL BLISTER UNIT IS OPEN OR TORN
SUN PHARMA